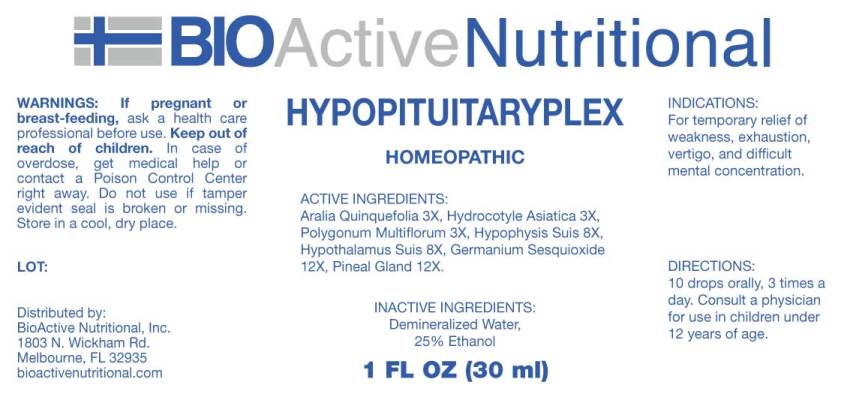 DRUG LABEL: Hypopituitaryplex
NDC: 43857-0031 | Form: LIQUID
Manufacturer: BioActive Nutritional, Inc.
Category: homeopathic | Type: HUMAN OTC DRUG LABEL
Date: 20180625

ACTIVE INGREDIENTS: AMERICAN GINSENG 3 [hp_X]/1 mL; CENTELLA ASIATICA 3 [hp_X]/1 mL; FALLOPIA MULTIFLORA ROOT 3 [hp_X]/1 mL; SUS SCROFA HYPOTHALAMUS 8 [hp_X]/1 mL; SUS SCROFA PITUITARY GLAND 8 [hp_X]/1 mL; GERMANIUM SESQUIOXIDE 12 [hp_X]/1 mL; SUS SCROFA PINEAL GLAND 12 [hp_X]/1 mL
INACTIVE INGREDIENTS: WATER; ALCOHOL

Drug Facts:

ACTIVE INGREDIENTS:

Aralia Quinquefolia 3X, Hydrocotyle Asiatica 3X, Polygonum Multiflorum 3X, Hypophysis Suis 8X, Hypothalamus Suis 8X, Germanium Sesquioxide 12X, Pineal Gland 12X.

INDICATIONS:

For temporary relief of weakness, exhaustion, vertigo, and difficult mental concentration.

WARNINGS:

If pregnant or breast-feeding, ask a health care professional before use.

Keep out of reach of children. In case of overdose, get medical help or contact a Poison Control Center right away.

Do not use if tamper evident seal is broken or missing.

Store in cool, dry place.

DIRECTIONS:

10 drops orally, 3 times a day. Consult a physician for use in children under 12 years of age.

INACTIVE INGREDIENTS:

Demineralized Water, 25% Ethanol.

Keep out of reach of children. In case of overdose, get medical help or contact a Poison Control Center right away.

INDICATIONS:

For temporary relief of weakness, exhaustion, vertigo, and difficult mental concentration.

QUESTIONS:

Distributed by:

BioActive Nutritional, Inc.

1803 N. Wickham Rd.

Melbourne, FL 32935

bioactivenutritional.com

PACKAGE LABEL DISPLAY:

BIOActive Nutritional
HYPOPITUITARYPLEX
HOMEOPATHIC
1 FL OZ (30 ml)